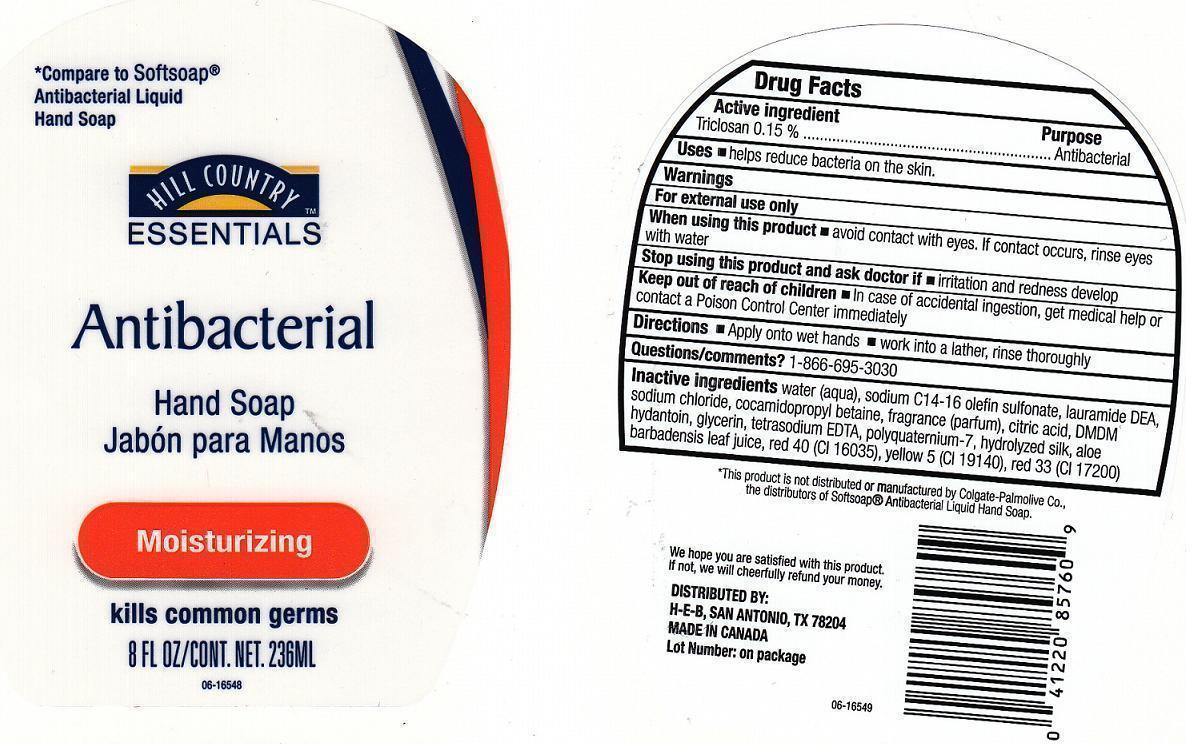 DRUG LABEL: HILL COUNTRY ESSENTIALS
NDC: 37808-215 | Form: LIQUID
Manufacturer: H.E.B.
Category: otc | Type: HUMAN OTC DRUG LABEL
Date: 20130115

ACTIVE INGREDIENTS: TRICLOSAN 1.5 mg/1 mL
INACTIVE INGREDIENTS: WATER; SODIUM C14-16 OLEFIN SULFONATE; LAURIC DIETHANOLAMIDE; SODIUM CHLORIDE; COCAMIDOPROPYL BETAINE; CITRIC ACID MONOHYDRATE; DMDM HYDANTOIN; GLYCERIN; EDETATE SODIUM; POLYQUATERNIUM-7 (70/30 ACRYLAMIDE/DADMAC; 1600000 MW); SILK, BASE HYDROLYZED (1000 MW); ALOE VERA LEAF; FD&C RED NO. 40; FD&C YELLOW NO. 5; D&C RED NO. 33

DRUG FACTS

ACTIVE INGREDIENT

TRICLOSAN 0.15%

PURPOSE

ANTIBACTERIAL

USES

HELPS REDUCE BACTERIA ON THE SKIN.

WARNINGS

FOR EXTERNAL USE ONLY

WHEN USING THIS PRODUCT

AVOID CONTACT WITH EYES. IF CONTACT OCCURS, RINSE EYES WITH WATER.

STOP USING THIS PRODUCT AND ASK DOCTOR IF

IRRITATION OR REDNESS DEVELOP.

KEEP OUT OF REACH OF CHILDREN

IN CASE OF ACCIDENTAL INGESTION, GET MEDICAL HELP OR CONTACT A POISON CONTROL CENTER IMMEDIATELY.

DIRECTIONS

APPLY ONTO WET HANDS. WORK INTO A LATHER, RINSE THOROUGHLY.

QUESTIONS/COMMENTS?

1-866-695-3030

INACTIVE INGREDIENTS

WATER (AQUA), SODIUM C14-16 OLEFIN SULFONATE, LAURAMIDE DEA, SODIUM CHLORIDE, COCAMIDOPROPYL BETAINE, FRAGRANCE (PARFUM), CITRIC ACID, DMDM HYDANTOIN, GLYCERIN, TETRASODIUM EDTA, POLYQUATERNIUM-7, HYDROLYZED SILK, ALOE BARBADENSIS LEAF JUICE, RED 40 (CI 16035), YELLOW 5 (CI 19140), RED 33 (CI 17200).